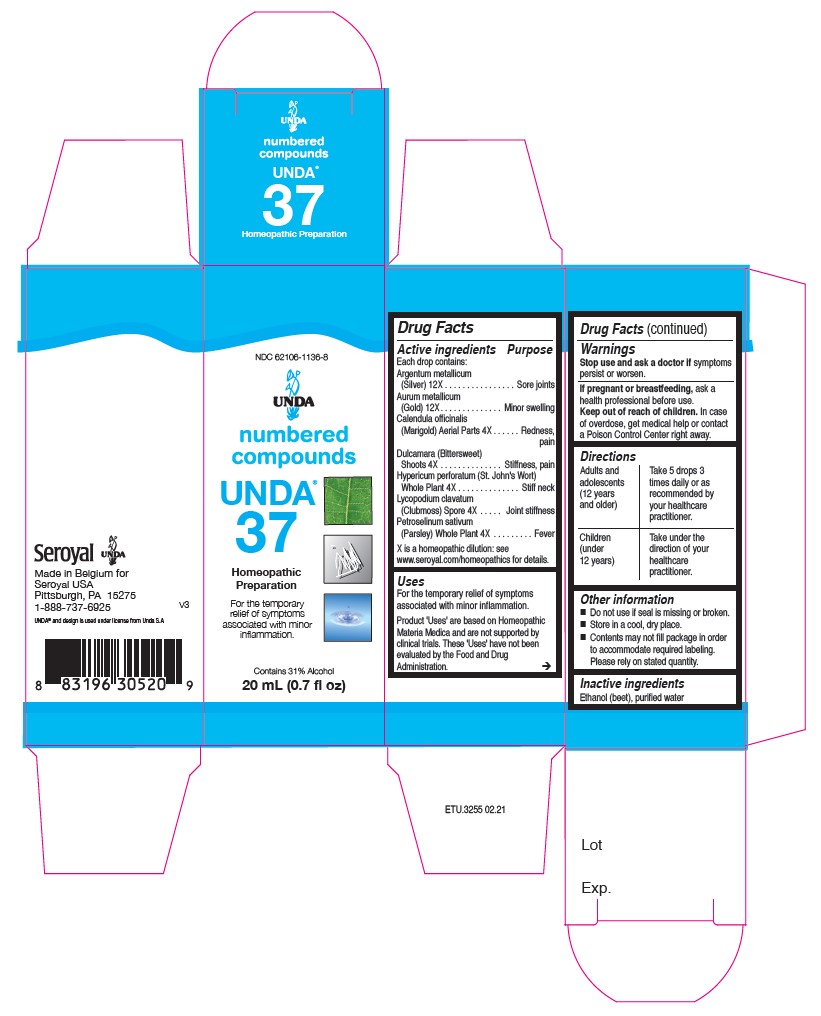 DRUG LABEL: Unda 37
NDC: 62106-1136 | Form: LIQUID
Manufacturer: Seroyal USA
Category: homeopathic | Type: HUMAN OTC DRUG LABEL
Date: 20210715

ACTIVE INGREDIENTS: SOLANUM DULCAMARA STEM 4 [hp_X]/20 mL; HYPERICUM PERFORATUM 4 [hp_X]/20 mL; GOLD 12 [hp_X]/20 mL; PETROSELINUM CRISPUM 4 [hp_X]/20 mL; CALENDULA OFFICINALIS FLOWERING TOP 4 [hp_X]/20 mL; SILVER 12 [hp_X]/20 mL; LYCOPODIUM CLAVATUM SPORE 4 [hp_X]/20 mL
INACTIVE INGREDIENTS: ALCOHOL; WATER

Unda 37

Active ingredients
Each drop contains:
Argentum metallicum (Silver) 12X
Aurum metallicum (Gold) 12X
Calendula officinalis (Marigold) Aerial Parts 4X
Dulcamara (Bittersweet) Shoots 4X
Hypericum perforatum (St. John’s Wort) Whole Plant 4X
Lycopodium clavatum (Clubmoss) Spore 4X
Petroselinum sativum (Parsley) Whole Plant 4X

Uses
For the temporary relief of symptoms associated with minor inflammation.

Warnings
Stop use and ask a doctor if symptoms persist or worsen.
If pregnant or breastfeeding, ask a health professional before use.
Keep out of reach of children. In case of overdose, get medical help or contact
a Poison Control Center right away.

Stop use and ask a doctor if symptoms persist or worsen.

PREGNANCY OR BREAST FEEDING

If pregnant or breastfeeding, ask a health professional before use.

Keep out of reach of children.

OVERDOSAGE

In case of overdose, get medical help or contact a
Poison Control Center right away.

Inactive Ingredients:

Ethanol (beet),
purified water

Other information

Do not use if seal is missing or broken.
Store in a cool, dry place.

Contents may not fill package in order
to accommodate required labeling.
Please rely on stated quantity.

Directions
Adults and adolescents (12 years and older)
Take 5 drops three times daily or as
recommended by your healthcare practitioner.

Children (under 12 years)

Take under the direction of your
healthcare practitioner.

Uses
For the temporary relief of symptoms associated with minor inflammation.

Directions
Adults and adolescents (12 years and older)
Take 5 drops three times daily or as recommended by your healthcare practitioner.

Children (under 12 years)

Take under the direction of your healthcare practitioner.

PACKAGE LABEL

NDC 62106-1136-8

UNDA

numbered compounds

UNDA 37

Homeopathic Preparation

For the temporary relief of symptoms
associated with minor inflammation.

Contains 31% Alcohol
0.7 fl oz (20 ml)